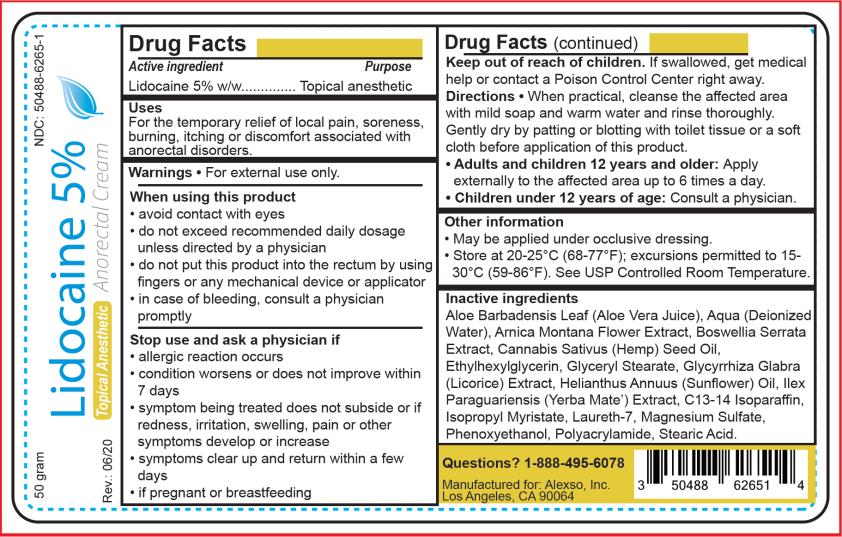 DRUG LABEL: Lidocaine 5 Percent
NDC: 50488-6265 | Form: CREAM
Manufacturer: Alexso, Inc
Category: otc | Type: HUMAN OTC DRUG LABEL
Date: 20200703

ACTIVE INGREDIENTS: LIDOCAINE 5 g/100 g
INACTIVE INGREDIENTS: ALOE VERA LEAF; WATER; ARNICA MONTANA FLOWER; INDIAN FRANKINCENSE; CANNABIS SATIVA SEED OIL; ETHYLHEXYLGLYCERIN; GLYCERYL MONOSTEARATE; GLYCYRRHIZA GLABRA; SUNFLOWER OIL; C13-14 ISOPARAFFIN; ISOPROPYL MYRISTATE; LAURETH-7; MAGNESIUM SULFATE, UNSPECIFIED; PHENOXYETHANOL; STEARIC ACID; ILEX PARAGUARIENSIS LEAF; POLYACRYLAMIDE (10000 MW)

Lidocaine 5_Percent Cream

LIDOCAINE - Lidocaine 5% anorectal cream
Alexso, Inc.

Disclaimer: Most OTC drugs are not reviewed and approved by FDA, however they may be marketed if they comply with applicable regulations and policies. FDA has not evaluated whether this product complies.

----------

Lidocaine 5% Anorectal Cream

Drug Facts

Active ingredient

Lidocaine 5% w/w

Purpose

Topical anesthetic

Uses

For the temporary relief of local pain, soreness, burning, itching or discomfort associated with anorectal disorders.

Warnings

For external use only.

When using this product

- avoid contact with eyes
- do not exceed recommended daily dosage unless directed by a physician
- do not put this product into the rectum by using fingers or any mechanical device or applicator
- in case of bleeding, consult a physician promptly

Stop use and ask a physician if

- allergic reaction occurs
- condition worsens or does not improve within 7 days
- symptom being treated does not subside or if redness, irritation, swelling, pain or other symptoms develop or increase
- symptoms clear up and return within a few days
- if pregnant or breastfeeding

Keep out of reach of children.

If swallowed, get medical help or contact a Poison Control Center right away.

Directions

When practical, cleanse the affected area with mild soap and warm water and rinse thoroughly. Gently dry by patting or blotting with toilet tissue or a soft cloth before application of this product.
Adults and children 12 years and older: Apply externally to the affected area up to 6 times a day.
Children under 12 years of age: Consult a physician.

Other information

- May be applied under occlusive dressing.
- Store at 20-25°C (68-77°F); excursions permitted to 15-30°C (59-86°F). See USP Controlled Room Temperature.

Inactive ingredients

Aloe Barbadensis Leaf (Aloe Vera Juice), Aqua (Deionized Water), Arnica Montana Flower Extract, Boswellia Serrata Extract, Cannabis Sativus (Hemp) Seed Oil, Ethylhexylglycerin, Glyceryl Stearate, Glycyrrhiza Glabra (Licorice) Extract, Helianthus Annuus (Sunflower) Oil, Ilex Paraguariensis (Yerba Mate) Extract, C13-14 Isoparaffin, Isopropyl Myristate, Laureth-7, Magnesium Sulfate, Phenoxyethanol, Polyacrylamide, Stearic Acid.

PRINCIPAL DISPLAY PANEL

Lidocaine 5% Cream

NDC 50488-6265-1

Lidocaine 5%

Anorectal Cream

Topical Anesthetic

50 grams

Manufactured for:

Alexso, Inc.

Los Angeles, CA 90064